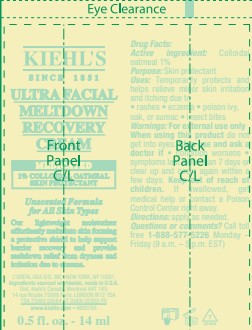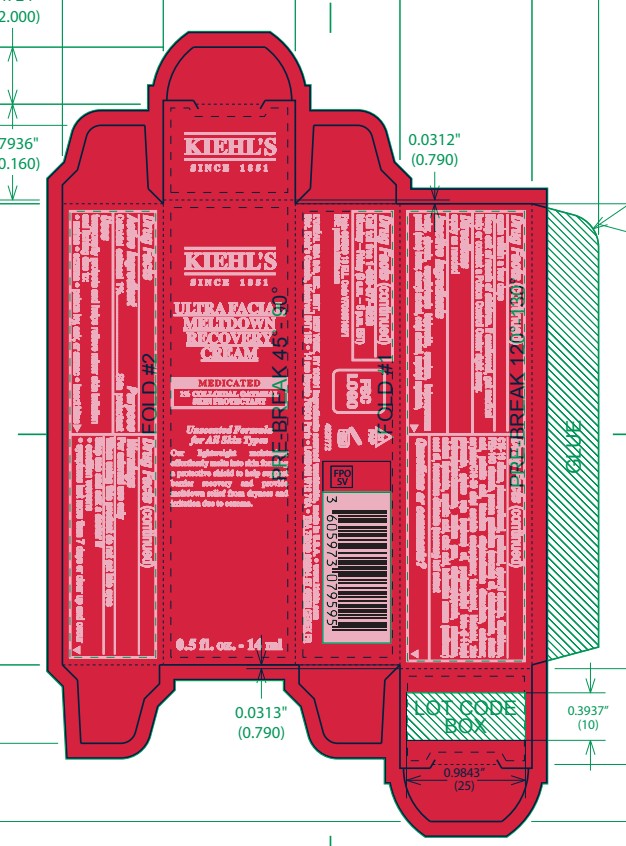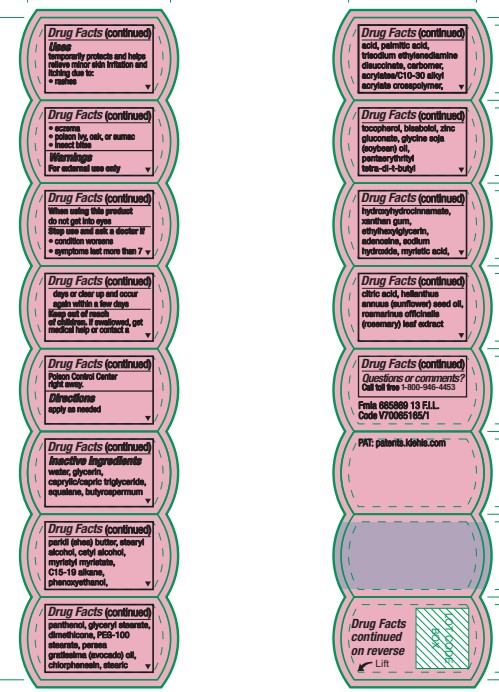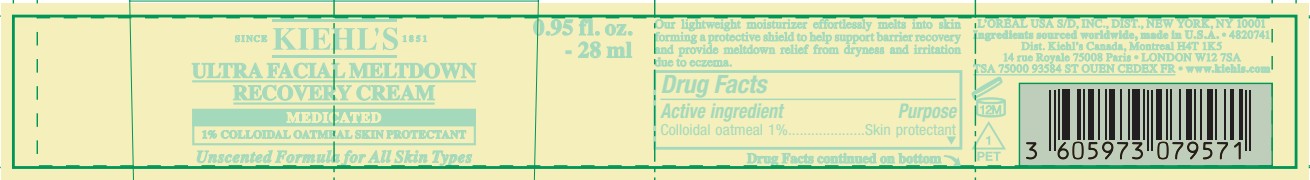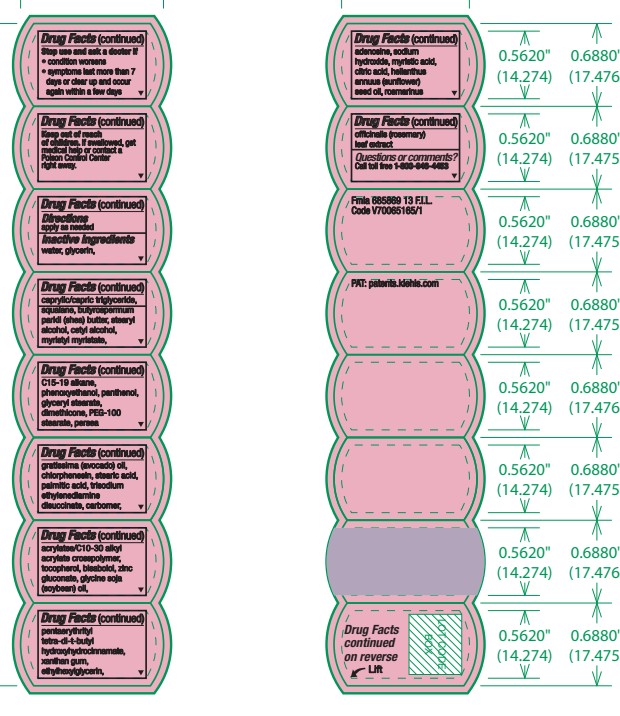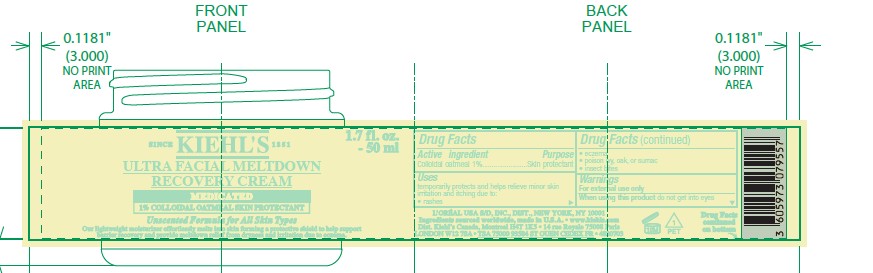 DRUG LABEL: KIEHLS SINCE 1851 Ultra Facial Meltdown Recovery
NDC: 49967-571 | Form: CREAM
Manufacturer: L’Oreal USA Products Inc
Category: otc | Type: HUMAN OTC DRUG LABEL
Date: 20250630

ACTIVE INGREDIENTS: OATMEAL 10 mg/1 mL
INACTIVE INGREDIENTS: WATER; GLYCERIN; CAPRYLIC/CAPRIC TRIGLYCERIDE; SQUALANE; BUTYROSPERMUM PARKII (SHEA) BUTTER; STEARYL ALCOHOL; CETYL ALCOHOL; MYRISTYL MYRISTATE; C15-19 ALKANE; PHENOXYETHANOL; PANTHENOL; GLYCERYL STEARATE; DIMETHICONE; PEG-100 STEARATE; PERSEA GRATISSIMA (AVOCADO) OIL; CHLORPHENESIN; STEARIC ACID; PALMITIC ACID; TRISODIUM ETHYLENEDIAMINE DISUCCINATE; CARBOMER; ACRYLATES/C10-30 ALKYL ACRYLATE CROSSPOLYMER (60000 MPA.S); TOCOPHEROL; BISABOLOL; ZINC GLUCONATE; SOYBEAN OIL; PENTAERYTHRITYL TETRA-DI-T-BUTYL HYDROXYHYDROCINNAMATE; XANTHAN GUM; ETHYLHEXYLGLYCERIN; ADENOSINE; SODIUM HYDROXIDE; MYRISTIC ACID; CITRIC ACID; HELIANTHUS ANNUUS (SUNFLOWER) SEED OIL; ROSEMARY

Drug Facts

Active ingredient

Colloidal oatmeal 1%

Purpose

Skin protectant

Uses

temporarily protects and helps relieve minor skin irritation and itching due to:

- rashes
- eczema
- poison ivy, oak, or sumac
- insect bites

Warnings

For external use only

When using this product

do not get into eyes

Stop use and ask a doctor if

• condition worsens
• symptoms last more than 7days or clear up and occur again within a few days

Keep out of reach of children.

If swallowed, get medical help or contact a Poison Control Center right away.

Directions

apply as needed

Inactive ingredients

Water, glycerin, caprylic/capric triglyceride, squalane, butyrospermum parkii (shea) butter, stearyl alcohol, cetyl alcohol, myristyl myristate, C15-19 alkane, phenoxyethanol, panthenol, glyceryl stearate, dimethicone, PEG-100 stearate, persea gratissima (avocado) oil, chlorphenesin, stearic acid, palmitic acid, trisodium ethylenediamine disuccinate, carbomer, acrylates/C10-30 alkyl acrylate crosspolymer, tocopherol, bisabolol, zinc gluconate, glycine soja (soybean) oil, pentaerythrityl tetra-di-t-butyl hydroxyhydrocinnamate, xanthan gum, ethylhexylglycerin, adenosine, sodium hydroxide, myristic acid, citric acid, helianthus annuus (sunflower) seed oil, rosmarinus officinalis (rosemary) leaf extract

Questions or comments?

Call toll free 1-800-946-4453